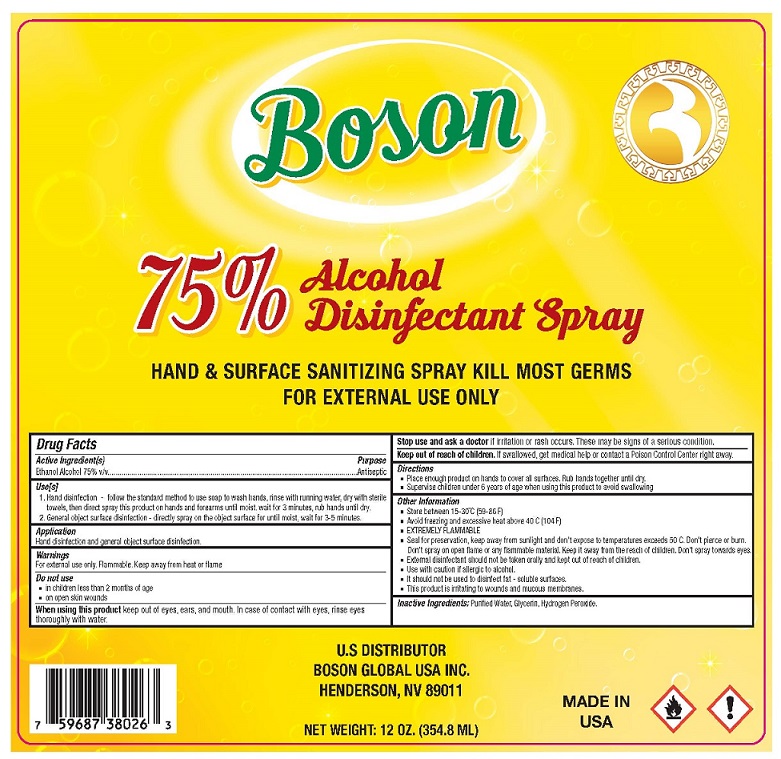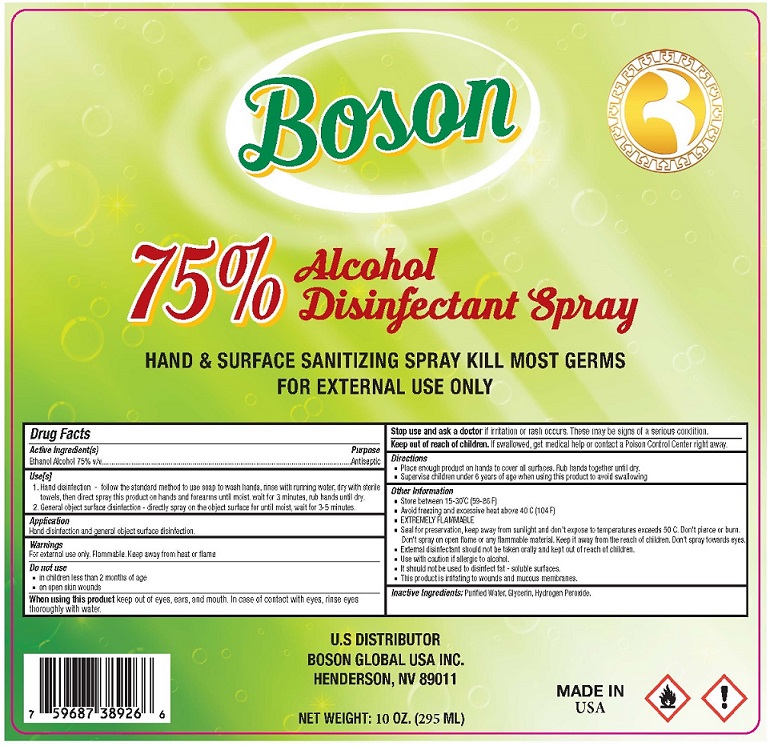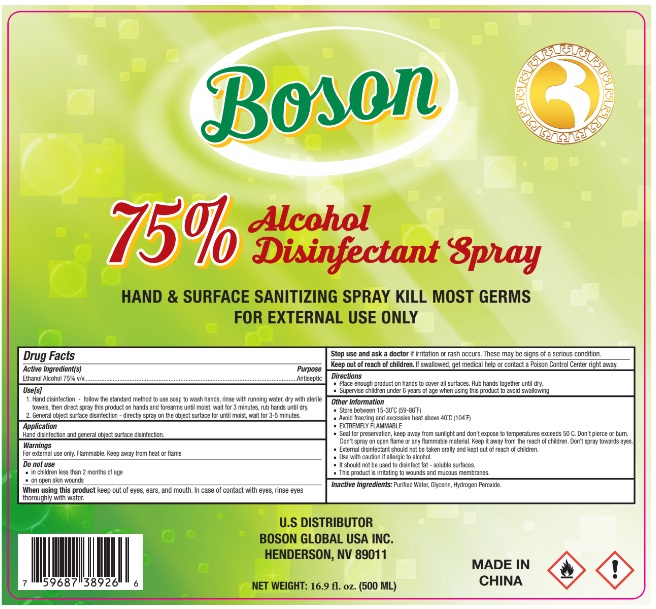 DRUG LABEL: Boson
NDC: 53325-125 | Form: SPRAY
Manufacturer: Aliml Nutritional Products, Inc.
Category: otc | Type: HUMAN OTC DRUG LABEL
Date: 20200729

ACTIVE INGREDIENTS: ALCOHOL 75 mL/100 mL
INACTIVE INGREDIENTS: GLYCERIN; HYDROGEN PEROXIDE; WATER

Active Ingredient

Ethanol Alcohol 75% v/v.

Purpose

Antiseptic

Use

1. Hand disinfection - follow the standard method to use soap to wash hands, rinse with running water, dry with sterile towel, then direct spray this product on hands and forearms until moist, wait for 3 minutes, rub hands until dry.
2. General object surface disinfection - directly spray on the object surface for until moist, waif for 3-5 minutes.

Warnings

For external use only - hands
Flammable, keep away from heat and flame
Do not use

- In children less than 2 months of age
- On open skin wound

When using the product

- keep out of eyes, in case of contact with eyes, flush thoroughly with water

Keep out of reach of children. If swallowed, get medical help or contact a Poison Control Center right away.

Directions

- Place enough product on hands to cover all surfaces. Rub hands together until dry.
- For children under 6, use only under adult supervision.
- Not recommended for infants.

Other information

- Store between 15-30C (59-86F)
- Avoid freezing and excessive heat above 40C (104F)
- Extremely flammable
- Seal for preservation, keep away from sunlight and don't expose to temperature exceeds 50C. Don't piece or burn
- Don't spray on open flame or any flammable material. Keep it away from the reach of children.
- Don't spray toward eyes
- External disinfectant should not be taken orally and kept out the reach of children
- Use with caution if allergic to alcohol
- It should not be used to disinfect fat-soluble surfaces
- The is product is irritating to wounds or mucous membranes

Inactive ingredients

Purified water, glycerin, Hydrogen peroxide